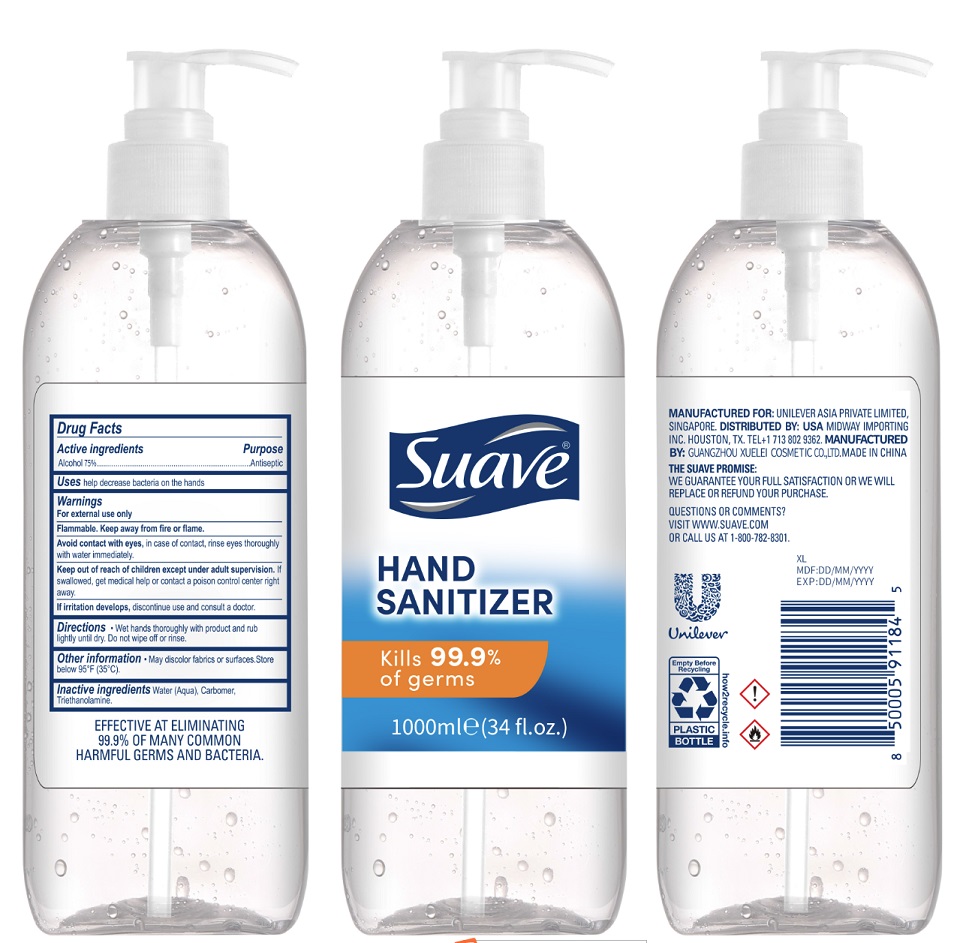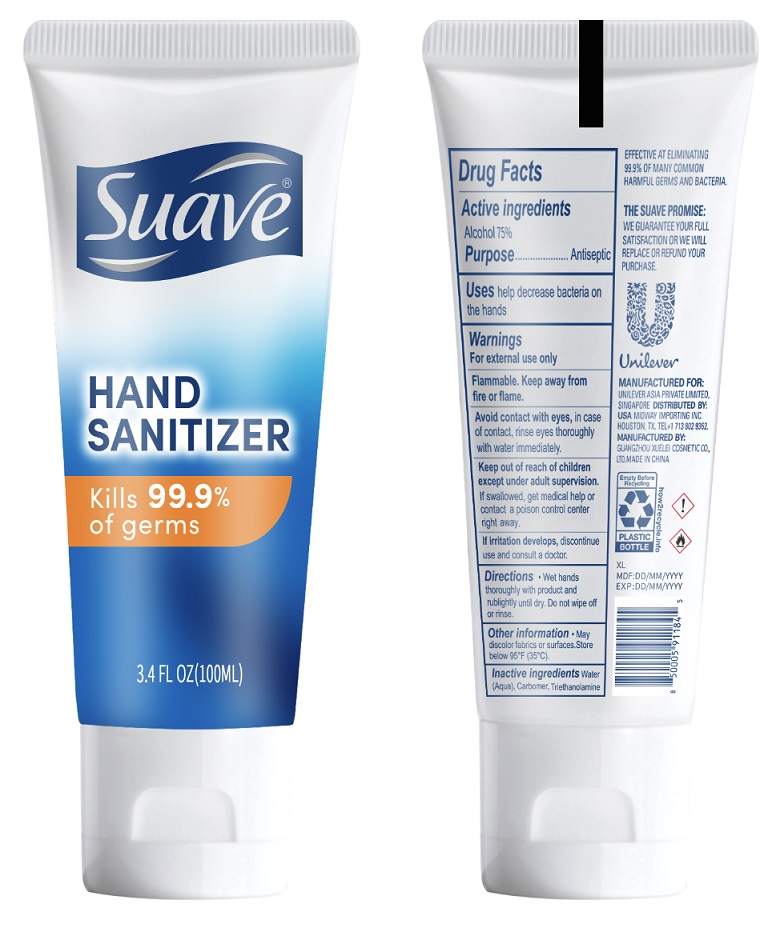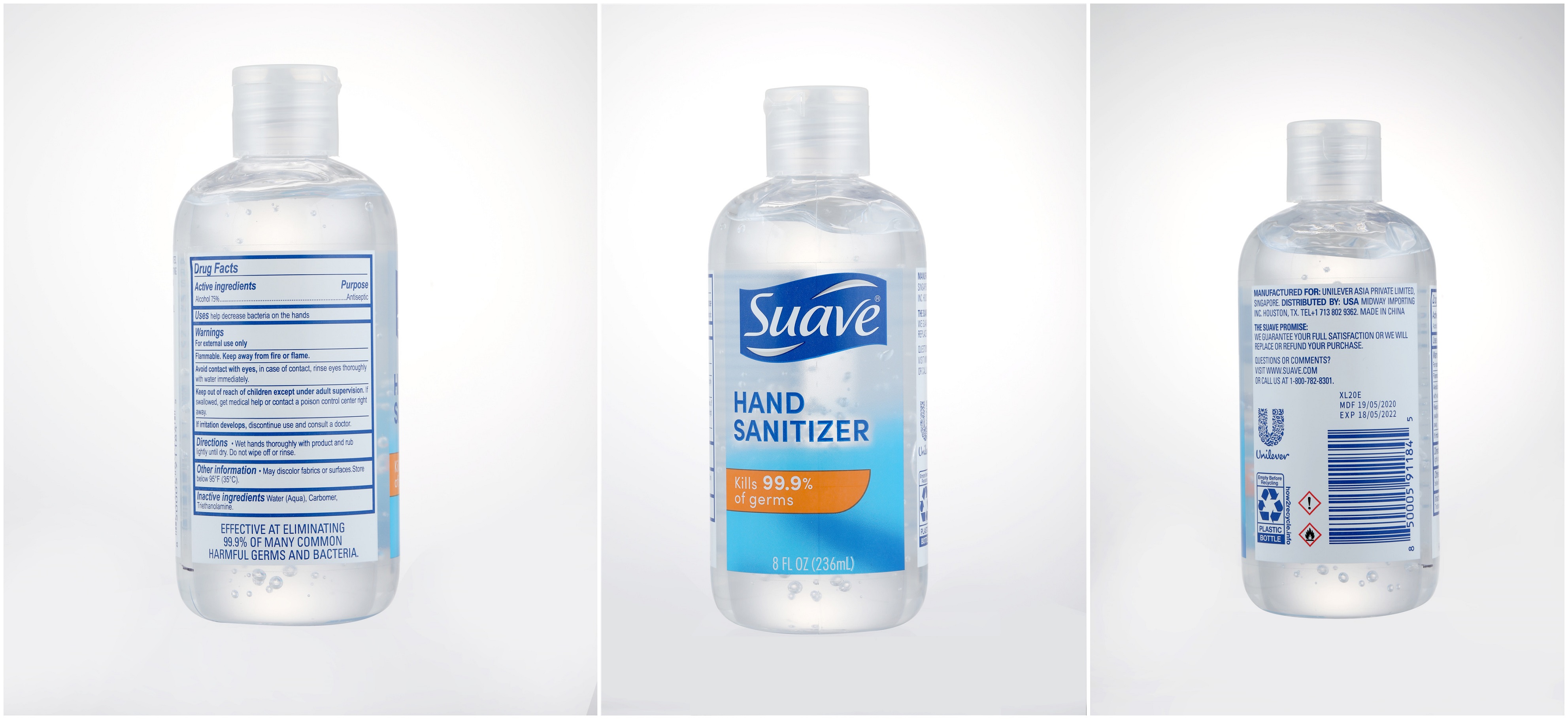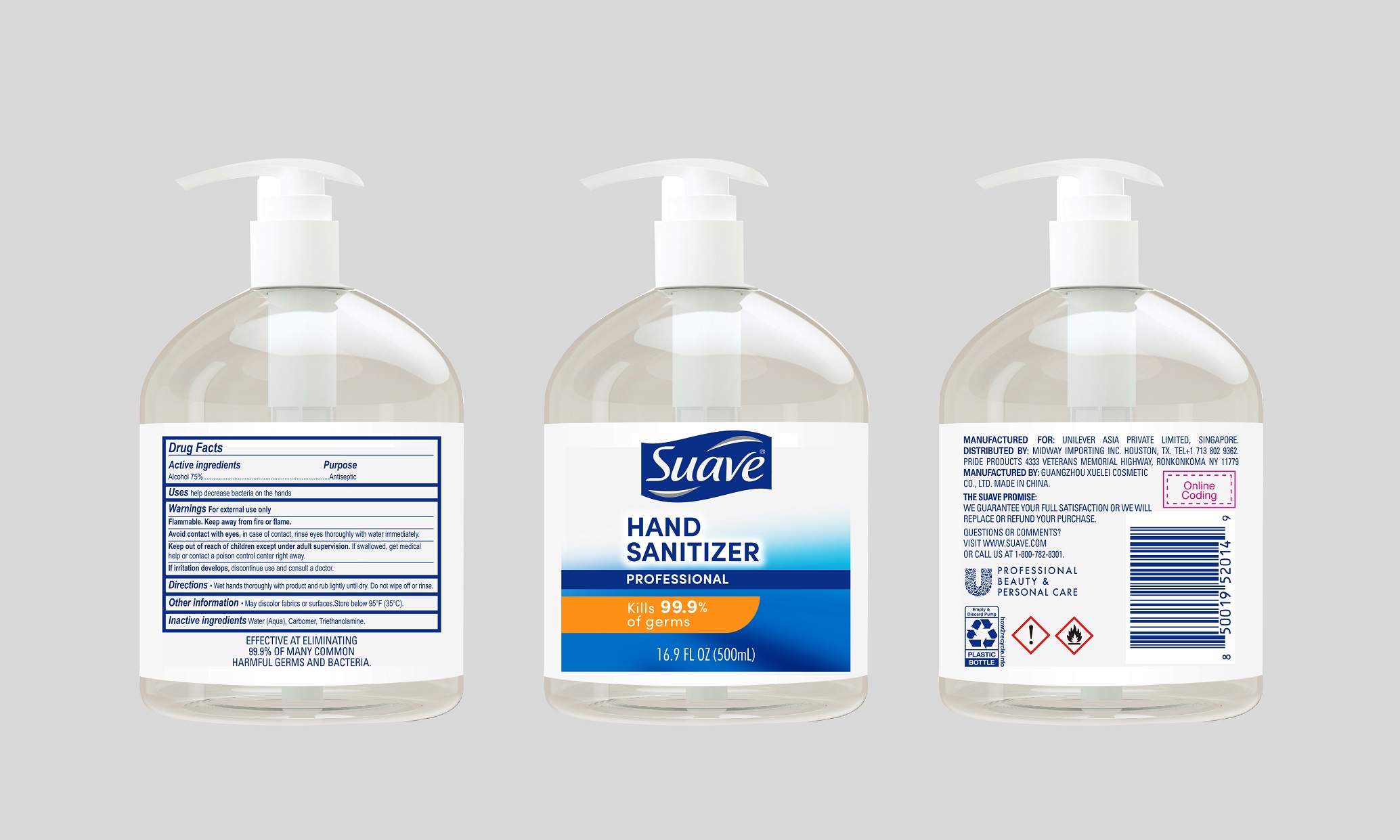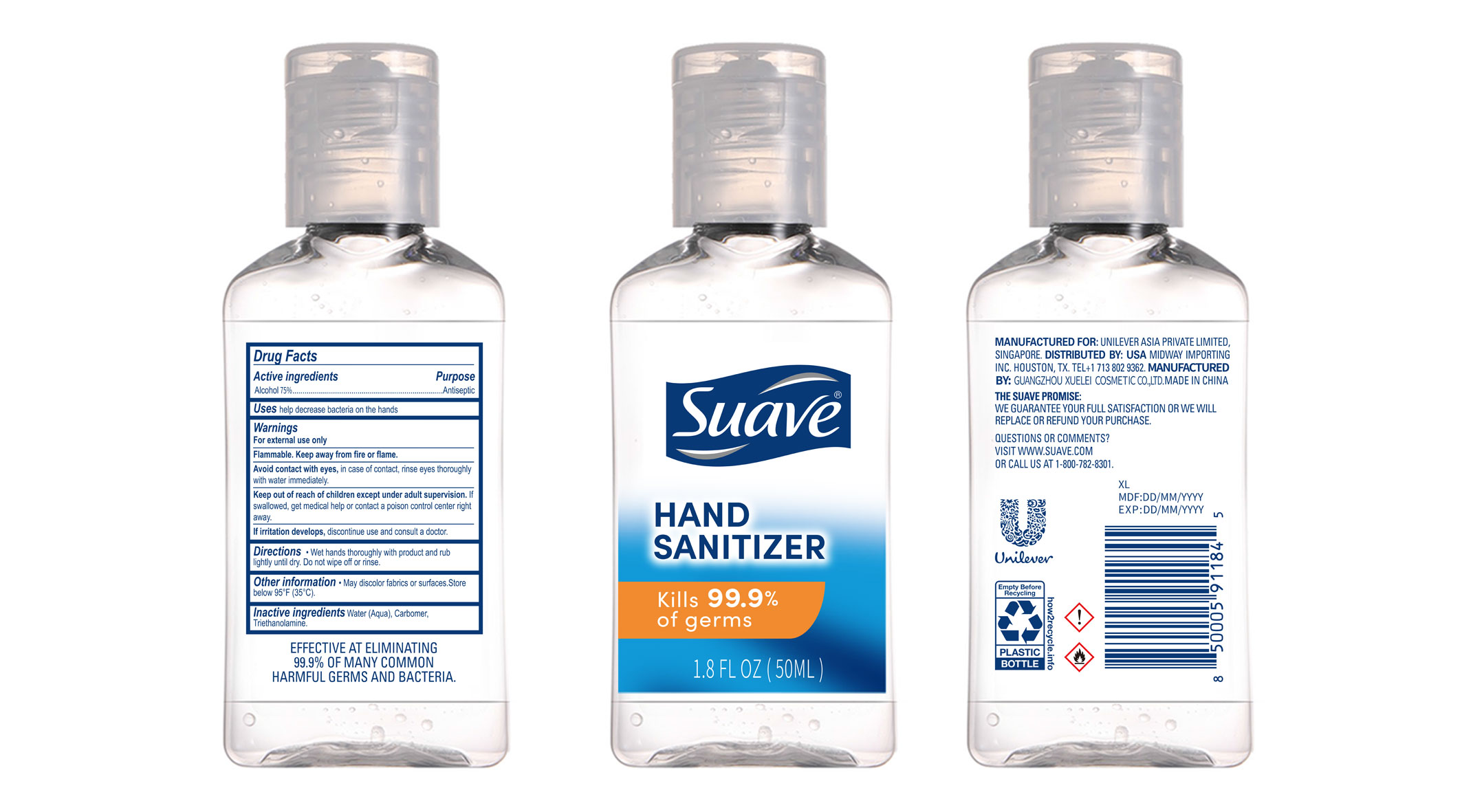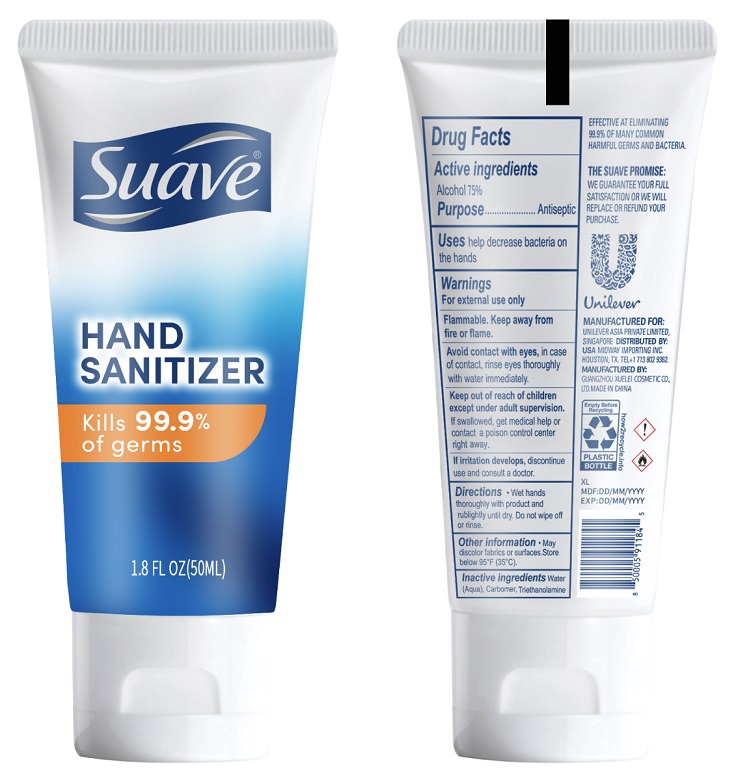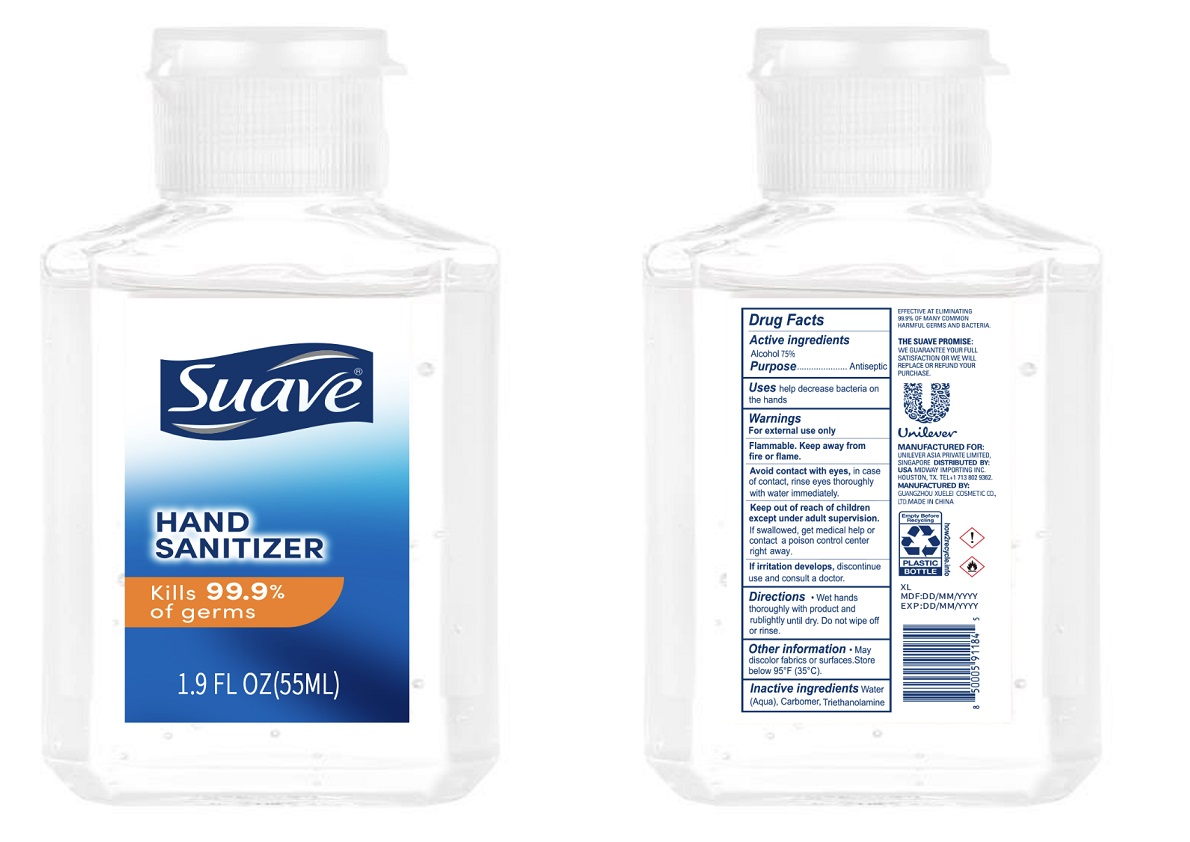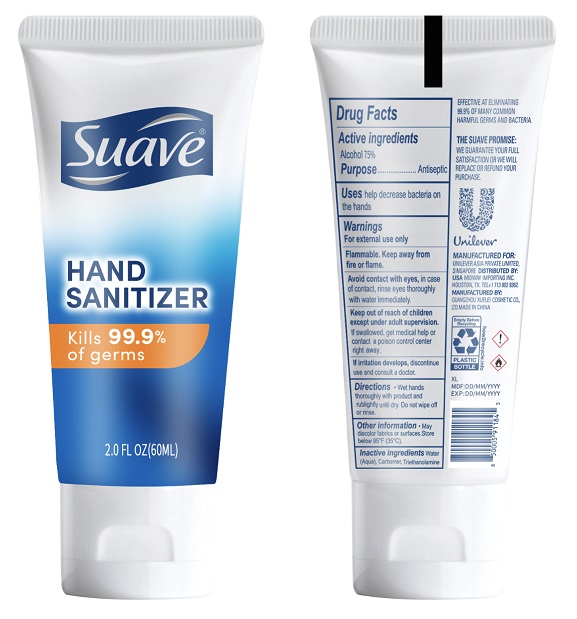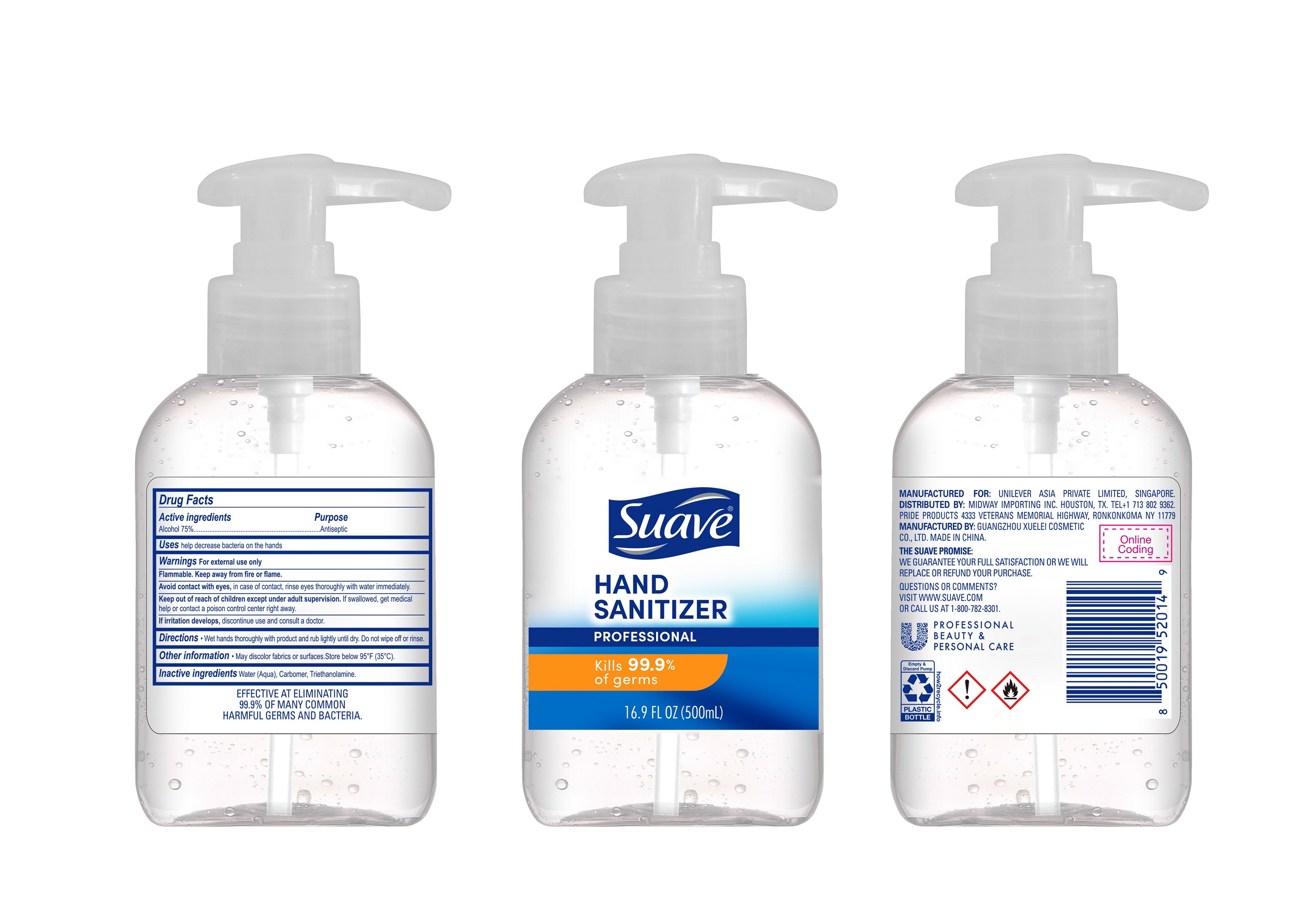 DRUG LABEL: Suave HAND SANITIZER
NDC: 76095-016 | Form: GEL
Manufacturer: Midway Importing, Inc.
Category: otc | Type: HUMAN OTC DRUG LABEL
Date: 20211108

ACTIVE INGREDIENTS: ALCOHOL 75 mL/100 mL
INACTIVE INGREDIENTS: WATER 22.19 g/100 mL; CARBOMER HOMOPOLYMER TYPE B (ALLYL PENTAERYTHRITOL CROSSLINKED) 0.4 g/100 mL; TROLAMINE 0.22 g/100 mL

Suave HAND SANITIZER

Active ingredients

Alcohol 75%

Purpose

Antiseptic

Uses

help decrease bacteriaon the hands

Warnings

For exteral use only

Flammable. Keep away from fire or flame.

Avoid contact with eyes, in case of contact. rinse eyes thoroughly with water immediately.

Keep out of reach of children except under adult supervision.If swallowed, get medical help or contact a poison control center right away.

If irritation develops, discontinue use and consult a doctor.

Keep out of reach of children except under adult supervision.If swallowed, get medical help or contact a poison control center right away.

Directions

Wet hands thoroughly with product and rub lightly until dry. Do not wipe off or rinse.

Other information

May discolor fabrics or surfaces. Store below 95°F（35℃）

Inactive ingredients

water （Aqua），Cartomer，Triethanolamine.

Package Label

Suave

HAND SANITIZER

Kills 99.9% of germs

1.8 FL OZ (50ML)

Package Label

Suave

HAND SANITIZER

Kills 99.9% of germs

1.9 FL OZ (55ML)

Package Label

Suave

HAND SANITIZER

Kills 99.9% of germs

2.0 FL OZ (60ML)

Package Label

Suave

HAND SANITIZER

Kills 99.9% of germs

3.4 FL OZ (100ML)

Package Label

Suave

HAND SANITIZER

Kills 99.9% of germs

8 FL OZ (236ML)

NDC: 76095-016-06

Package Label

500ml NDC: 76095-016-07

Package Label

Suave

HAND SANITIZER

Kills 99.9% of germs

500ml e (17 fl.oz.)

NDC: 76095-016-08

Package Label

Suave

HAND SANITIZER

Kills 99.9% of germs

1000ml e (34 fl.oz.)